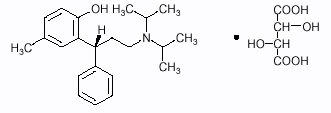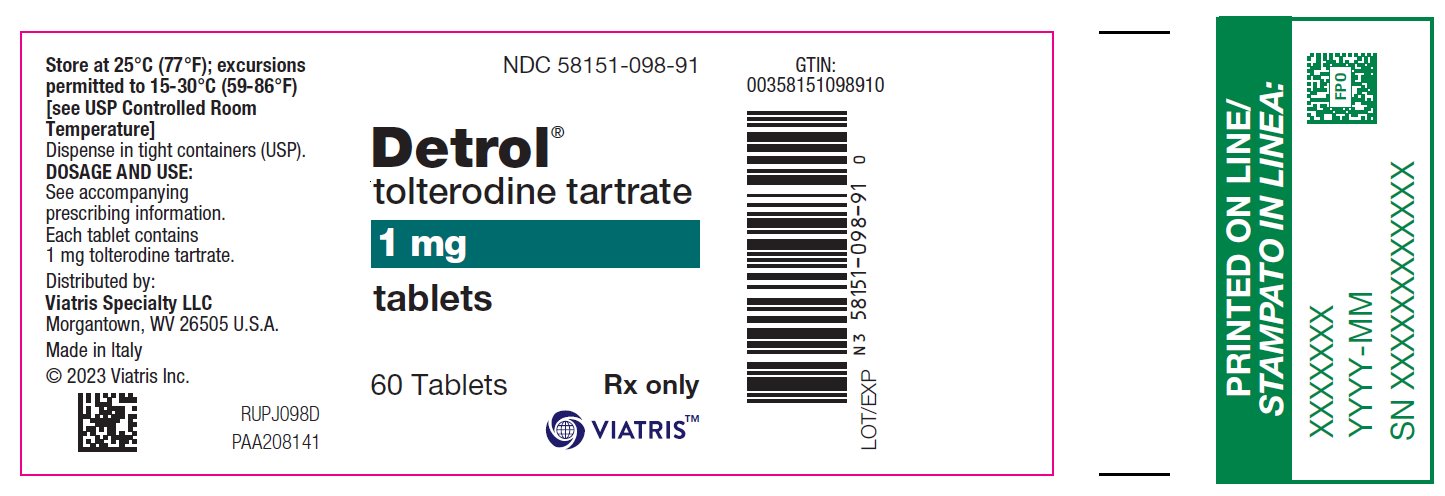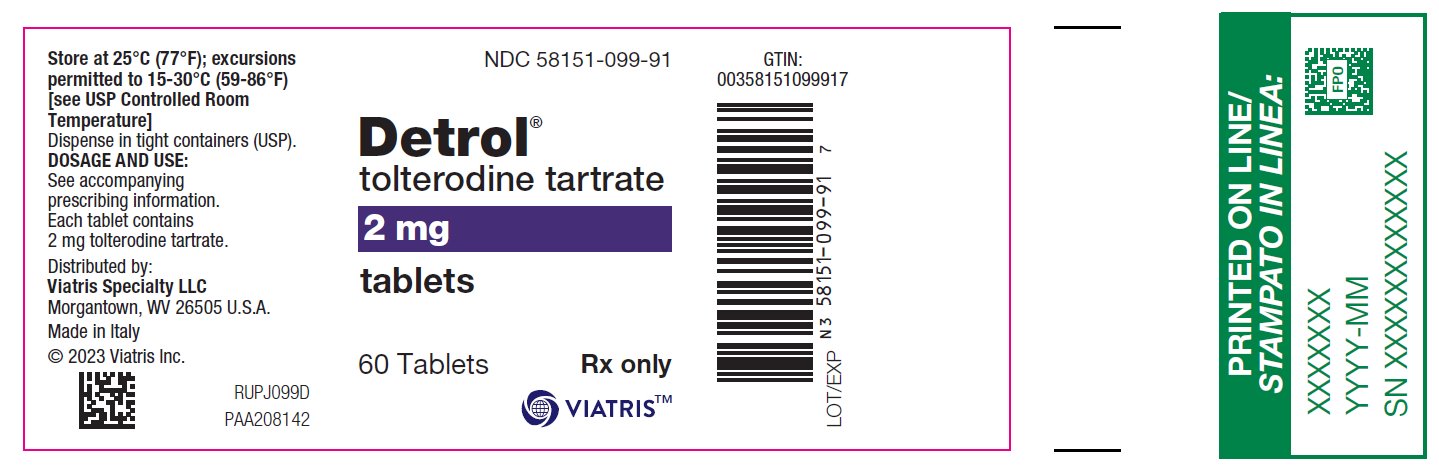 DRUG LABEL: Detrol
NDC: 58151-098 | Form: TABLET, FILM COATED
Manufacturer: Viatris Specialty LLC
Category: prescription | Type: HUMAN PRESCRIPTION DRUG LABEL
Date: 20230215

ACTIVE INGREDIENTS: TOLTERODINE TARTRATE 1 mg/1 1
INACTIVE INGREDIENTS: SILICON DIOXIDE; DIBASIC CALCIUM PHOSPHATE DIHYDRATE; MICROCRYSTALLINE CELLULOSE; HYPROMELLOSE, UNSPECIFIED; MAGNESIUM STEARATE; SODIUM STARCH GLYCOLATE TYPE A POTATO; STEARIC ACID; TITANIUM DIOXIDE

DESCRIPTION

DETROL Tablets contain tolterodine tartrate. The active moiety, tolterodine, is a muscarinic receptor antagonist. The chemical name of tolterodine tartrate is (R)-2-[3-[bis(1-methylethyl)-amino]1-phenylpropyl]-4-methylphenol [R-(R*,R*)]-2,3dihydroxybutanedioate (1:1) (salt). The empirical formula of tolterodine tartrate is C26H37NO7, and its molecular weight is 475.6. The structural formula of tolterodine tartrate is represented below:

Tolterodine tartrate is a white, crystalline powder. The pKa value is 9.87 and the solubility in water is 12 mg/mL. It is soluble in methanol, slightly soluble in ethanol, and practically insoluble in toluene. The partition coefficient (Log D) between n-octanol and water is 1.83 at pH 7.3.

DETROL Tablets for oral administration contain 1 or 2 mg of tolterodine tartrate. The inactive ingredients are colloidal anhydrous silica, calcium hydrogen phosphate dihydrate, cellulose microcrystalline, hypromellose, magnesium stearate, sodium starch glycolate (pH 3.0 to 5.0), stearic acid, and titanium dioxide.

CLINICAL PHARMACOLOGY

Tolterodine is a competitive muscarinic receptor antagonist. Both urinary bladder contraction and salivation are mediated via cholinergic muscarinic receptors.

After oral administration, tolterodine is metabolized in the liver, resulting in the formation of the 5-hydroxymethyl derivative, a major pharmacologically active metabolite. The 5-hydroxymethyl metabolite, which exhibits an antimuscarinic activity similar to that of tolterodine, contributes significantly to the therapeutic effect. Both tolterodine and the 5-hydroxymethyl metabolite exhibit a high specificity for muscarinic receptors, since both show negligible activity or affinity for other neurotransmitter receptors and other potential cellular targets, such as calcium channels.

Tolterodine has a pronounced effect on bladder function. Effects on urodynamic parameters before and 1 and 5 hours after a single 6.4 mg dose of tolterodine immediate release were determined in healthy volunteers. The main effects of tolterodine at 1 and 5 hours were an increase in residual urine, reflecting an incomplete emptying of the bladder, and a decrease in detrusor pressure. These findings are consistent with an antimuscarinic action on the lower urinary tract.

Pharmacokinetics

Absorption

In a study with ^14C-tolterodine solution in healthy volunteers who received a 5 mg oral dose, at least 77% of the radiolabeled dose was absorbed. Tolterodine immediate release is rapidly absorbed, and maximum serum concentrations (Cmax)typically occur within 1 to 2 hours after dose administration. Cmax and area under the concentration-time curve (AUC) determined after dosage of tolterodine immediate release are dose-proportional over the range of 1 to 4 mg.

Effect of Food

Food intake increases the bioavailability of tolterodine (average increase 53%), but does not affect the levels of the 5-hydroxymethyl metabolite in extensive metabolizers. This change is not expected to be a safety concern and adjustment of dose is not needed.

Distribution

Tolterodine is highly bound to plasma proteins, primarily α1-acid glycoprotein. Unbound concentrations of tolterodine average 3.7% ± 0.13% over the concentration range achieved in clinical studies. The 5-hydroxymethyl metabolite is not extensively protein bound, with unbound fraction concentrations averaging 36% ± 4.0%. The blood to serum ratio of tolterodine and the 5-hydroxymethyl metabolite averages 0.6 and 0.8, respectively, indicating that these compounds do not distribute extensively into erythrocytes. The volume of distribution of tolterodine following administration of a 1.28 mg intravenous dose is 113 ± 26.7 L.

Metabolism

Tolterodine is extensively metabolized by the liver following oral dosing. The primary metabolic route involves the oxidation of the 5-methyl group and is mediated by the cytochrome P450 2D6 (CYP2D6) and leads to the formation of a pharmacologically active 5-hydroxymethyl metabolite. Further metabolism leads to formation of the 5-carboxylic acid and N-dealkylated 5-carboxylic acid metabolites, which account for 51% ± 14% and 29% ± 6.3% of the metabolites recovered in the urine, respectively.

Variability in Metabolism

A subset (about 7%) of the population is devoid of CYP2D6, the enzyme responsible for the formation of the 5-hydroxymethyl metabolite of tolterodine. The identified pathway of metabolism for these individuals (“poor metabolizers”) is dealkylation via cytochrome P450 3A4 (CYP3A4) to N-dealkylated tolterodine. The remainder of the population is referred to as “extensive metabolizers.” Pharmacokinetic studies revealed that tolterodine is metabolized at a slower rate in poor metabolizers than in extensive metabolizers; this results in significantly higher serum concentrations of tolterodine and in negligible concentrations of the 5-hydroxymethyl metabolite.

Excretion

Following administration of a 5 mg oral dose of ^14C-tolterodine solution to healthy volunteers, 77% of radioactivity was recovered in urine and 17% was recovered in feces in 7 days. Less than 1% (<2.5% in poor metabolizers) of the dose was recovered as intact tolterodine, and 5% to 14% (<1% in poor metabolizers) was recovered as the active 5-hydroxymethyl metabolite.

A summary of mean (± standard deviation) pharmacokinetic parameters of tolterodine immediate release and the 5-hydroxymethyl metabolite in extensive (EM) and poor (PM) metabolizers is provided in Table 1. These data were obtained following single and multiple doses of tolterodine 4 mg administered twice daily to 16 healthy male volunteers (8 EM, 8 PM).

Table 1. Summary of Mean (±SD) Pharmacokinetic Parameters of Tolterodine and its Active Metabolite (5-hydroxymethyl metabolite) in Healthy Volunteers
 | Tolterodine |  |  |  |  | 5-Hydroxymethyl Metabolite
Phenotype; (CYP2D6) | tmax; (h) | Cmax [Parameter was dose-normalized from 4 mg to 2 mg.]; (µg/L) | Cavg; (µg/L) | t1/2; (h) | CL/F; (L/h) | tmax; (h) | Cmax; (µg/L) | Cavg; (µg/L) | t1/2; (h)
Single-dose; EM; PM | 1.6±1.5; 1.4±0.5 | 1.6±1.2; 10±4.9 | 0.50±0.35; 8.3±4.3 | 2.0±0.7; 6.5±1.6 | 534±697; 17±7.3 | 1.8±1.4; [= not applicable.] | 1.8±0.7 | 0.62±0.26 | 3.1±0.7
Multiple-dose; EM; PM | 1.2±0.5; 1.9±1.0 | 2.6±2.8; 19±7.5 | 0.58±0.54; 12±5.1 | 2.2±0.4; 9.6±1.5 | 415±377; 11±4.2 | 1.2±0.5 | 2.4±1.3 | 0.92±0.46 | 2.9±0.4
Cmax = Maximum plasma concentration; tmax = Time of occurrence of Cmax;
Cavg = Average plasma concentration; t1/2 = Terminal elimination half-life; CL/F = Apparent oral clearance.
EM = Extensive metabolizers; PM = Poor metabolizers.

Pharmacokinetics in Special Populations

Age

In Phase 1, multiple-dose studies in which tolterodine immediate release 4 mg (2 mg bid) was administered, serum concentrations of tolterodine and of the 5-hydroxymethyl metabolite were similar in healthy elderly volunteers (aged 64 through 80 years) and healthy young volunteers (aged less than 40 years). In another Phase 1 study, elderly volunteers (aged 71 through 81 years) were given tolterodine immediate release 2 or 4 mg (1 or 2 mg bid). Mean serum concentrations of tolterodine and the 5-hydroxymethyl metabolite in these elderly volunteers were approximately 20% and 50% higher, respectively, than reported in young healthy volunteers. However, no overall differences were observed in safety between older and younger patients on tolterodine in Phase 3, 12-week, controlled clinical studies; therefore, no tolterodine dosage adjustment for elderly patients is recommended (see PRECAUTIONS, Geriatric Use).

Pediatric

The pharmacokinetics of tolterodine have not been established in pediatric patients.

Gender

The pharmacokinetics of tolterodine immediate release and the 5-hydroxymethyl metabolite are not influenced by gender. Mean Cmax of tolterodine (1.6 µg/L in males versus 2.2 µg/L in females) and the active 5-hydroxymethyl metabolite (2.2 µg/L in males versus 2.5 µg/L in females) are similar in males and females who were administered tolterodine immediate release 2 mg. Mean AUC values of tolterodine (6.7 µg·h/L in males versus 7.8 µg·h/L in females) and the 5-hydroxymethyl metabolite (10 µg·h/L in males versus 11 µg·h/L in females) are also similar. The elimination half-life of tolterodine for both males and females is 2.4 hours, and the half-life of the 5-hydroxymethyl metabolite is 3.0 hours in females and 3.3 hours in males.

Race

Pharmacokinetic differences due to race have not been established.

Renal Insufficiency

Renal impairment can significantly alter the disposition of tolterodine immediate release and its metabolites. In a study conducted in patients with creatinine clearance between 10 and 30 mL/min, tolterodine immediate release and the 5-hydroxymethyl metabolite levels were approximately 2–3 fold higher in patients with renal impairment than in healthy volunteers. Exposure levels of other metabolites of tolterodine (e.g., tolterodine acid, N-dealkylated tolterodine acid, N-dealkylated tolterodine, and N-dealkylated hydroxylated tolterodine) were significantly higher (10–30 fold) in renally impaired patients as compared to the healthy volunteers. The recommended dosage for patients with significantly reduced renal function is DETROL 1 mg twice daily (see PRECAUTIONS, General and DOSAGE AND ADMINISTRATION).

Hepatic Insufficiency

Liver impairment can significantly alter the disposition of tolterodine immediate release. In a study conducted in cirrhotic patients, the elimination half-life of tolterodine immediate release was longer in cirrhotic patients (mean, 7.8 hours) than in healthy, young, and elderly volunteers (mean, 2 to 4 hours). The clearance of orally administered tolterodine was substantially lower in cirrhotic patients (1.0 ± 1.7 L/h/kg) than in the healthy volunteers (5.7 ± 3.8 L/h/kg). The recommended dose for patients with significantly reduced hepatic function is DETROL 1 mg twice daily (see PRECAUTIONS, General and DOSAGE AND ADMINISTRATION).

Drug-Drug Interactions

Fluoxetine

Fluoxetine is a selective serotonin reuptake inhibitor and a potent inhibitor of CYP2D6 activity. In a study to assess the effect of fluoxetine on the pharmacokinetics of tolterodine immediate release and its metabolites, it was observed that fluoxetine significantly inhibited the metabolism of tolterodine immediate release in extensive metabolizers, resulting in a 4.8-fold increase in tolterodine AUC. There was a 52% decrease in Cmax and a 20% decrease in AUC of the 5-hydroxymethyl metabolite. Fluoxetine thus alters the pharmacokinetics in patients who would otherwise be extensive metabolizers of tolterodine immediate release to resemble the pharmacokinetic profile in poor metabolizers. The sums of unbound serum concentrations of tolterodine immediate release and the 5-hydroxymethyl metabolite are only 25% higher during the interaction. No dose adjustment is required when DETROL and fluoxetine are coadministered.

Other Drugs Metabolized by Cytochrome P450 Isoenzymes

Tolterodine immediate release does not cause clinically significant interactions with other drugs metabolized by the major drug metabolizing CYP enzymes. In vivo drug-interaction data show that tolterodine immediate release does not result in clinically relevant inhibition of CYP1A2, 2D6, 2C9, 2C19, or 3A4 as evidenced by lack of influence on the marker drugs caffeine, debrisoquine, S-warfarin, and omeprazole. In vitro data show that tolterodine immediate release is a competitive inhibitor of CYP2D6 at high concentrations (Ki 1.05 µM), while tolterodine immediate release as well as the 5-hydroxymethyl metabolite are devoid of any significant inhibitory potential regarding the other isoenzymes.

CYP3A4 Inhibitors

The effect of 200 mg daily dose of ketoconazole on the pharmacokinetics of tolterodine immediate release was studied in 8 healthy volunteers, all of whom were poor metabolizers (see Pharmacokinetics, Variability in Metabolism for discussion of poor metabolizers). In the presence of ketoconazole, the mean Cmax and AUC of tolterodine increased by 2 and 2.5 fold, respectively. Based on these findings, other potent CYP3A inhibitors such as other azole antifungals (e.g., itraconazole, miconazole) or macrolide antibiotics (e.g., erythromycin, clarithromycin) or cyclosporine or vinblastine may also lead to increases of tolterodine plasma concentrations (see PRECAUTIONS and DOSAGE AND ADMINISTRATION).

Warfarin

In healthy volunteers, coadministration of tolterodine immediate release 4 mg (2 mg bid) for 7 days and a single dose of warfarin 25 mg on day 4 had no effect on prothrombin time, Factor VII suppression, or on the pharmacokinetics of warfarin.

Oral Contraceptives

Tolterodine immediate release 4 mg (2 mg bid) had no effect on the pharmacokinetics of an oral contraceptive (ethinyl estradiol 30 µg/levonorgestrel 150 µg) as evidenced by the monitoring of ethinyl estradiol and levonorgestrel over a 2-month cycle in healthy female volunteers.

Diuretics

Coadministration of tolterodine immediate release up to 8 mg (4 mg bid) for up to 12 weeks with diuretic agents, such as indapamide, hydrochlorothiazide, triamterene, bendroflumethiazide, chlorothiazide, methylchlorothiazide, or furosemide, did not cause any adverse electrocardiographic (ECG) effects.

Cardiac Electrophysiology

The effect of 2 mg BID and 4 mg BID of tolterodine immediate release (IR) on the QT interval was evaluated in a 4-way crossover, double-blind, placebo- and active-controlled (moxifloxacin 400 mg QD) study in healthy male (N=25) and female (N=23) volunteers aged 18–55 years. Study subjects [approximately equal representation of CYP2D6 extensive metabolizers (EMs) and poor metabolizers (PMs)] completed sequential 4-day periods of dosing with moxifloxacin 400 mg QD, tolterodine 2 mg BID, tolterodine 4 mg BID, and placebo. The 4 mg BID dose of tolterodine IR (two times the highest recommended dose) was chosen because this dose results in tolterodine exposure similar to that observed upon coadministration of tolterodine 2 mg BID with potent CYP3A4 inhibitors in patients who are CYP2D6 poor metabolizers (see PRECAUTIONS, Drug Interactions). QT interval was measured over a 12-hour period following dosing, including the time of peak plasma concentration (Tmax) of tolterodine and at steady state (Day 4 of dosing).

Table 2 summarizes the mean change from baseline to steady state in corrected QT interval (QTc) relative to placebo at the time of peak tolterodine (1 hour) and moxifloxacin (2 hour) concentrations. Both Fridericia’s (QTcF) and a population-specific (QTcP) method were used to correct QT interval for heart rate. No single QT correction method is known to be more valid than others. QT interval was measured manually and by machine, and data from both are presented. The mean increase of heart rate associated with a 4 mg/day dose of tolterodine in this study was 2.0 beats/minute and 6.3 beats/minute with 8 mg/day tolterodine. The change in heart rate with moxifloxacin was 0.5 beats/minute.

Table 2. Mean (CI) change in QTc from baseline to steady state (Day 4 of dosing) at Tmax (relative to placebo)
Drug/Dose | N | QTcF; (msec) (manual) | QTcF; (msec); (machine) | QTcP; (msec); (manual) | QTcP; (msec); (machine)
Tolterodine; 2 mg BID [At Tmax of 1 hr; 95% Confidence Interval] | 48 | 5.01; (0.28, 9.74) | 1.16; (-2.99, 5.30) | 4.45; (-0.37, 9.26) | 2.00; (-1.81, 5.81)
Tolterodine; 4 mg BID | 48 | 11.84; (7.11, 16.58) | 5.63; (1.48, 9.77) | 10.31; (5.49, 15.12) | 8.34; (4.53, 12.15)
Moxifloxacin 400 mg QD [At Tmax of 2 hr; 90% Confidence Interval] | 45 | 19.26 [The effect on QT interval with 4 days of moxifloxacin dosing in this QT trial may be greater than typically observed in QT trials of other drugs.]; (15.49, 23.03) | 8.90; (4.77, 13.03) | 19.10; (15.32, 22.89) | 9.29; (5.34, 13.24)

The reason for the difference between machine and manual read of QT interval is unclear.

The QT effect of tolterodine immediate release tablets appeared greater for 8 mg/day (two times the therapeutic dose) compared to 4 mg/day. The effect of tolterodine 8 mg/day was not as large as that observed after four days of therapeutic dosing with the active control moxifloxacin. However, the confidence intervals overlapped.

Tolterodine’s effect on QT interval was found to correlate with plasma concentration of tolterodine. There appeared to be a greater QTc interval increase in CYP2D6 poor metabolizers than in CYP2D6 extensive metabolizers after tolterodine treatment in this study.

This study was not designed to make direct statistical comparisons between drugs or dose levels. There has been no association of Torsade de Pointes in the international post-marketing experience with DETROL or DETROL LA (see PRECAUTIONS, Patients with Congenital or Acquired QT Prolongation).

CLINICAL STUDIES

DETROL Tablets were evaluated for the treatment of overactive bladder with symptoms of urge urinary incontinence, urgency, and frequency in four randomized, double-blind, placebo-controlled, 12-week studies. A total of 853 patients received DETROL 2 mg twice daily and 685 patients received placebo. The majority of patients were Caucasian (95%) and female (78%), with a mean age of 60 years (range, 19 to 93 years). At study entry, nearly all patients perceived they had urgency and most patients had increased frequency of micturitions and urge incontinence. These characteristics were well balanced across treatment groups for the studies.

The efficacy endpoints for study 007 (see Table 3) included the change from baseline for:

- Number of incontinence episodes per week
- Number of micturitions per 24 hours (averaged over 7 days)
- Volume of urine voided per micturition (averaged over 2 days)

The efficacy endpoints for studies 008, 009, and 010 (see Table 4) were identical to the above endpoints with the exception that the number of incontinence episodes was per 24 hours (averaged over 7 days).

Table 3. 95% Confidence Intervals (CI) for the Difference between DETROL (2 mg bid) and Placebo for the Mean Change at Week 12 from Baseline in Study 007
 | DETROL; (SD); N=514 | Placebo; (SD); N=508 | Difference; (95% CI)
Number of Incontinence Episodes per Week; Mean baseline; Mean change from baseline | 23.2; -10.6 (17) | 23.3; -6.9 (15) | -3.7 (-5.7, -1.6)
Number of Micturitions per 24 Hours; Mean baseline; Mean change from baseline | 11.1; -1.7 (3.3) | 11.3; -1.2 (2.9) | -0.5 [The difference between DETROL and placebo was statistically significant.] (-0.9, -0.1)
Volume Voided per Micturition (mL); Mean baseline; Mean change from baseline | 137; 29 (47) | 136; 14 (41) | 15 (9, 21)
SD = Standard Deviation.

Table 4. 95% Confidence Intervals (CI) for the Difference between DETROL (2 mg bid) and Placebo for the Mean Change at Week 12 from Baseline in Studies 008, 009, 010
Study |  | DETROL; (SD) | Placebo; (SD) | Difference; (95% CI)
Number of Incontinence Episodes per 24 Hours
008 | Number of patients; Mean baseline; Mean change from baseline | 93; 2.9; -1.3 (3.2) | 40; 3.3; -0.9 (1.5) | 0.5 (-1.3,0.3)
009 | Number of patients; Mean baseline; Mean change from baseline | 116; 3.6; -1.7 (2.5) | 55; 3.5; -1.3 (2.5) | -0.4 (-1.0,0.2)
010 | Number of patients; Mean baseline; Mean change from baseline | 90; 3.7; -1.6 (2.4) | 50; 3.5; -1.1 (2.1) | -0.5 (-1.1,0.1)
Number of Micturitions per 24 Hours
008 | Number of patients; Mean baseline; Mean change from baseline | 118; 11.5; -2.7 (3.8) | 56; 11.7; -1.6 (3.6) | -1.2 [The difference between DETROL and placebo was statistically significant.] (-2.0,-0.4)
009 | Number of patients; Mean baseline; Mean change from baseline | 128; 11.2; -2.3 (2.1) | 64; 11.3; -1.4 (2.8) | -0.9 (-1.5,-0.3)
010 | Number of patients; Mean baseline; Mean change from baseline | 108; 11.6; -1.7 (2.3) | 56; 11.6; -1.4 (2.8) | -0.38 (-1.1,0.3)
Volume Voided per Micturition (mL)
008 | Number of patients; Mean baseline; Mean change from baseline | 118; 166; 38 (54) | 56; 157; 6 (42) | 32 (18,46)
009 | Number of patients; Mean baseline; Mean change from baseline | 129; 155; 36 (50) | 64; 158; 10 (47) | 26 (14,38)
010 | Number of patients; Mean baseline; Mean change from baseline | 108; 155; 31 (45) | 56; 160; 13 (52) | 18 (4,32)
SD = Standard Deviation.

INDICATIONS AND USAGE

DETROL Tablets are indicated for the treatment of overactive bladder with symptoms of urge urinary incontinence, urgency, and frequency.

CONTRAINDICATIONS

DETROL Tablets are contraindicated in patients with urinary retention, gastric retention, or uncontrolled narrow-angle glaucoma. DETROL is also contraindicated in patients who have demonstrated hypersensitivity to the drug or its ingredients, or to fesoterodine fumarate extended-release tablets which, like DETROL, are metabolized to 5-hydroxymethyl tolterodine.

WARNINGS

Anaphylaxis and angioedema requiring hospitalization and emergency medical treatment have occurred with the first or subsequent doses of DETROL. In the event of difficulty in breathing, upper airway obstruction, or fall in blood pressure, DETROL should be discontinued and appropriate therapy promptly provided.

PRECAUTIONS

General

Risk of Urinary Retention and Gastric Retention

DETROL Tablets should be administered with caution to patients with clinically significant bladder outflow obstruction because of the risk of urinary retention and to patients with gastrointestinal obstructive disorders, such as pyloric stenosis, because of the risk of gastric retention (see CONTRAINDICATIONS).

Decreased Gastrointestinal Motility

DETROL, like other antimuscarinic drugs, should be used with caution in patients with decreased gastrointestinal motility.

Controlled Narrow-Angle Glaucoma

DETROL should be used with caution in patients being treated for narrow-angle glaucoma.

Central Nervous System (CNS) Effects

Detrol is associated with anticholinergic central nervous system (CNS) effects including dizziness and somnolence (see ADVERSE REACTIONS). Patients should be monitored for signs of anticholinergic CNS effects, particularly after beginning treatment or increasing the dose. Advise patients not to drive or operate heavy machinery until the drug’s effects have been determined. If a patient experiences anticholinergic CNS effects, dose reduction or drug discontinuation should be considered.

Reduced Hepatic and Renal Function

For patients with significantly reduced hepatic function or renal function, the recommended dose of DETROL is 1 mg twice daily (see CLINICAL PHARMACOLOGY, Pharmacokinetics in Special Populations).

Myasthenia Gravis

DETROL should be used with caution in patients with myasthenia gravis, a disease characterized by decreased cholinergic activity at the neuromuscular junction.

Patients with Congenital or Acquired QT Prolongation

In a study of the effect of tolterodine immediate release tablets on the QT interval (see CLINICAL PHARMACOLOGY, Cardiac Electrophysiology), the effect on the QT interval appeared greater for 8 mg/day (two times the therapeutic dose) compared to 4 mg/day and was more pronounced in CYP2D6 poor metabolizers (PM) than extensive metabolizers (EMs). The effect of tolterodine 8 mg/day was not as large as that observed after four days of therapeutic dosing with the active control moxifloxacin. However, the confidence intervals overlapped. These observations should be considered in clinical decisions to prescribe DETROL for patients with a known history of QT prolongation or patients who are taking Class IA (e.g., quinidine, procainamide) or Class III (e.g., amiodarone, sotalol) antiarrhythmic medications (see PRECAUTIONS, Drug Interactions). There has been no association of Torsade de Pointes in the international post-marketing experience with DETROL or DETROL LA.

Information for Patients

Patients should be informed that antimuscarinic agents such as DETROL may produce the following effects: blurred vision, dizziness, or drowsiness. Patients should be advised to exercise caution in decisions to engage in potentially dangerous activities until the drug's effects have been determined.

Drug Interactions

CYP3A4 Inhibitors

Ketoconazole, an inhibitor of the drug metabolizing enzyme CYP3A4, significantly increased plasma concentrations of tolterodine when coadministered to subjects who were poor metabolizers (see CLINICAL PHARMACOLOGY, Variability in Metabolism and Drug-Drug Interactions).For patients receiving ketoconazole or other potent CYP3A4 inhibitors such as other azole antifungals (e.g., itraconazole, miconazole) or macrolide antibiotics (e.g., erythromycin, clarithromycin) or cyclosporine or vinblastine, the recommended dose of DETROL is 1 mg twice daily (see DOSAGE AND ADMINISTRATION).

Drug-Laboratory-Test Interactions

Interactions between tolterodine and laboratory tests have not been studied.

Carcinogenesis, Mutagenesis, Impairment of Fertility

Carcinogenicity studies with tolterodine were conducted in mice and rats. At the maximum tolerated dose in mice (30 mg/kg/day), female rats (20 mg/kg/day), and male rats (30 mg/kg/day), AUC values obtained for tolterodine were 355, 291, and 462 µg·h/L, respectively. In comparison, the human AUC value for a 2 mg dose administered twice daily is estimated at 34 µg·h/L. Thus, tolterodine exposure in the carcinogenicity studies was 9- to 14-fold higher than expected in humans. No increase in tumors was found in either mice or rats.

No mutagenic effects of tolterodine were detected in a battery of in vitro tests, including bacterial mutation assays (Ames test) in 4 strains of Salmonella typhimurium and in 2 strains of Escherichia coli, a gene mutation assay in L5178Y mouse lymphoma cells, and chromosomal aberration tests in human lymphocytes. Tolterodine was also negative in vivo in the bone marrow micronucleus test in the mouse.

In female mice treated for 2 weeks before mating and during gestation with 20 mg/kg/day (corresponding to AUC value of about 500 µg·h/L), neither effects on reproductive performance or fertility were seen. Based on AUC values, the systemic exposure was about 15-fold higher in animals than in humans. In male mice, a dose of 30 mg/kg/day did not induce any adverse effects on fertility.

Pregnancy

Tolterodine, administered at oral doses of 20 mg/kg/day (approximately 14 times the human exposure), showed no anomalies or malformations in mice. When given at doses of 30 to 40 mg/kg/day, tolterodine has been shown to be embryolethal, reduce fetal weight, and increase the incidence of fetal abnormalities (cleft palate, digital abnormalities, intra-abdominal hemorrhage, and various skeletal abnormalities, primarily reduced ossification) in mice. At these doses, the AUC values were about 20- to 25-fold higher than in humans. Rabbits treated subcutaneously at a dose of 0.8 mg/kg/day achieved an AUC of 100 µg·h/L, which is about 3-fold higher than that resulting from the human dose. This dose did not result in any embryotoxicity or teratogenicity. There are no studies of tolterodine in pregnant women. Therefore, DETROL should be used during pregnancy only if the potential benefit for the mother justifies the potential risk to the fetus.

Nursing Mothers

Tolterodine is excreted into the milk in mice. Offspring of female mice treated with tolterodine 20 mg/kg/day during the lactation period had slightly reduced body weight gain. The offspring regained the weight during the maturation phase. It is not known whether tolterodine is excreted in human milk; therefore, DETROL should not be administered during nursing. A decision should be made whether to discontinue nursing or to discontinue DETROL in nursing mothers.

Pediatric Use

Efficacy in the pediatric population has not been demonstrated.

Two pediatric phase 3 randomized, placebo-controlled, double-blind, 12-week studies were conducted using tolterodine extended release (DETROL LA) capsules. A total of 710 pediatric patients (486 on DETROL LA and 224 on placebo) aged 5–10 years with urinary frequency and urge urinary incontinence were studied. The percentage of patients with urinary tract infections was higher in patients treated with DETROL LA (6.6%) compared to patients who received placebo (4.5%). Aggressive, abnormal, and hyperactive behavior and attention disorders occurred in 2.9% of children treated with DETROL LA compared to 0.9% of children treated with placebo.

Geriatric Use

Of the 1120 patients who were treated in the four Phase 3, 12-week clinical studies of DETROL, 474 (42%) were 65 to 91 years of age. No overall differences in safety were observed between the older and younger patients (see CLINICAL PHARMACOLOGY, Pharmacokinetics in Special Populations).

ADVERSE REACTIONS

The Phase 2 and 3 clinical trial program for DETROL Tablets included 3071 patients who were treated with DETROL (N=2133) or placebo (N=938). The patients were treated with 1, 2, 4, or 8 mg/day for up to 12 months. No differences in the safety profile of tolterodine were identified based on age, gender, race, or metabolism.

The data described below reflect exposure to DETROL 2 mg bid in 986 patients and to placebo in 683 patients exposed for 12 weeks in five Phase 3, controlled clinical studies. Because clinical trials are conducted under widely varying conditions, adverse reaction rates observed in the clinical trials of a drug cannot be directly compared to rates in the clinical trials of another drug and may not reflect the rates observed in practice. The adverse reaction information from clinical trials does, however, provide a basis for identifying the adverse events that appear to be related to drug use and approximating rates.

Sixty-six percent of patients receiving DETROL 2 mg bid reported adverse events versus 56% of placebo patients. The most common adverse events reported by patients receiving DETROL were dry mouth, headache, constipation, vertigo/dizziness, and abdominal pain. Dry mouth, constipation, abnormal vision (accommodation abnormalities), urinary retention, and xerophthalmia are expected side effects of antimuscarinic agents.

Dry mouth was the most frequently reported adverse event for patients treated with DETROL 2 mg bid in the Phase 3 clinical studies, occurring in 34.8% of patients treated with DETROL and 9.8% of placebo-treated patients. One percent of patients treated with DETROL discontinued treatment due to dry mouth.

The frequency of discontinuation due to adverse events was highest during the first 4 weeks of treatment. Seven percent of patients treated with DETROL 2 mg bid discontinued treatment due to adverse events versus 6% of placebo patients. The most common adverse events leading to discontinuation of DETROL were dizziness and headache.

Three percent of patients treated with DETROL 2 mg bid reported a serious adverse event versus 4% of placebo patients. Significant ECG changes in QT and QTc have not been demonstrated in clinical-study patients treated with DETROL 2 mg bid. Table 5 lists the adverse events reported in 1% or more of the patients treated with DETROL 2 mg bid in the 12-week studies. The adverse events are reported regardless of causality.

Table 5. Incidence [in nearest integer.] (%) of Adverse Events Exceeding Placebo Rate and Reported in >1% of Patients Treated with DETROL Tablets (2 mg bid) in 12-week, Phase 3 Clinical Studies
Body System | Adverse Event | % DETROL N=986 | % Placebo N=683
Autonomic Nervous | accommodation abnormal dry mouth | 2 35 | 1 10
General | chest pain fatigue headache influenza-like symptoms | 2 4 7 3 | 1 3 5 2
Central/Peripheral Nervous | vertigo/dizziness | 5 | 3
Gastrointestinal | abdominal pain constipation diarrhea dyspepsia | 5 7 4 4 | 3 4 3 1
Urinary | dysuria | 2 | 1
Skin/Appendages | dry skin | 1 | 0
Musculoskeletal | arthralgia | 2 | 1
Vision | xerophthalmia | 3 | 2
Psychiatric | somnolence | 3 | 2
Metabolic/Nutritional | weight gain | 1 | 0
Resistance Mechanism | infection | 1 | 0

Post-marketing Surveillance

The following events have been reported in association with tolterodine use in worldwide post-marketing experience: General: anaphylaxis and angioedema; Cardiovascular: tachycardia, palpitations, peripheral edema; Central/Peripheral Nervous: confusion, disorientation, memory impairment, hallucinations.

Reports of aggravation of symptoms of dementia (e.g., confusion, disorientation, delusion) have been reported after tolterodine therapy was initiated in patients taking cholinesterase inhibitors for the treatment of dementia.

Because these spontaneously reported events are from the worldwide post-marketing experience, the frequency of events and the role of tolterodine in their causation cannot be reliably determined.

OVERDOSAGE

A 27-month-old child who ingested 5 to 7 DETROL Tablets 2 mg was treated with a suspension of activated charcoal and was hospitalized overnight with symptoms of dry mouth. The child fully recovered.

Management of Overdosage

Overdosage with DETROL can potentially result in severe central anticholinergic effects and should be treated accordingly.

ECG monitoring is recommended in the event of overdosage. In dogs, changes in the QT interval (slight prolongation of 10% to 20%) were observed at a suprapharmacologic dose of 4.5 mg/kg, which is about 68 times higher than the recommended human dose. In clinical trials of normal volunteers and patients, QT interval prolongation was observed with tolterodine immediate release at doses up to 8 mg (4 mg bid) and higher doses were not evaluated (see PRECAUTIONS, Patients with Congenital or Acquired QT Prolongation).

DOSAGE AND ADMINISTRATION

The initial recommended dose of DETROL Tablets is 2 mg twice daily. The dose may be lowered to 1 mg twice daily based on individual response and tolerability. For patients with significantly reduced hepatic or renal function or who are currently taking drugs that are potent inhibitors of CYP3A4, the recommended dose of DETROL is 1 mg twice daily (see PRECAUTIONS, General, PRECAUTIONS, Reduced Hepatic and Renal Function, and PRECAUTIONS, Drug Interactions).

HOW SUPPLIED

DETROL Tablets 1 mg (white, round, biconvex, film-coated tablets engraved with arcs above and below the letters “TO”) and DETROL Tablets 2 mg (white, round, biconvex, film-coated tablets engraved with arcs above and below the letters “DT”) are supplied as follows:

Bottles of 60
1 mg NDC 58151-098-91
2 mg NDC 58151-099-91

Store at 25ºC (77ºF); excursions permitted to 15–30ºC (59–86ºF) [see USP Controlled Room Temperature] (DTL).

Distributed by:
Viatris Specialty LLC
Morgantown, WV 26505 U.S.A.

Made in Italy

© 2023 Viatris Inc.

DETROL is a registered trademark of Viatris Specialty LLC, a Viatris Company.

The brands listed are trademarks of their respective owners.

UPJ:DTRLT:R1

Revised: 2/2023

PATIENT INFORMATION

DETROL®(DE-trol)
(tolterodine tartrate tablets)

Read the Patient Information that comes with DETROL before you start using it and each time you get a refill. There may be new information. This leaflet does not take the place of talking with your doctor about your condition or your treatment. Only your doctor can determine if treatment with DETROL is right for you.

What is DETROL?

DETROL is a prescription medicine for adults used to treat the following symptoms due to a condition called overactive bladder:

- Urge urinary incontinence: a strong need to urinate with leaking or wetting accidents
- Urgency: a strong need to urinate right away
- Frequency: urinating often

DETROL LA (tolterodine tartrate extended release capsules) did not help the symptoms of overactive bladder when studied in children.

What is overactive bladder?

Overactive bladder happens when you cannot control your bladder muscle. When the muscle contracts too often or cannot be controlled, you get symptoms of overactive bladder, which are leakage of urine (urge urinary incontinence), needing to urinate right away (urgency), and needing to urinate often (frequency).

Who should not take DETROL?

Do not take DETROL if you:

- Are not able to empty your bladder (urinary retention)
- Have delayed or slow emptying of your stomach (gastric retention)
- Have an eye problem called “uncontrolled narrow-angle glaucoma”
- Are allergic to DETROL or to any of its ingredients. See the end of this leaflet for a complete list of ingredients
- Are allergic to TOVIAZ which contains fesoterodine.

What should I tell my doctor before starting DETROL?

Before starting DETROL, tell your doctor about all of your medical and other conditions that may affect the use of DETROL, including:

- Stomach or intestinal problems or problems with constipation
- Problems emptying your bladder or if you have a weak urine stream
- Treatment for an eye problem called narrow-angle glaucoma
- Liver problems
- Kidney problems
- A condition called myasthenia gravis
- If you or any family members have a rare heart condition called QT prolongation (long QT syndrome)
- If you are pregnant or trying to become pregnant. It is not known if DETROL could harm your unborn baby.
- If you are breastfeeding.It is not known if DETROL passes into your breast milk or if it can harm your baby. Talk to your doctor about the best way to feed your baby if you take DETROL.

Tell your doctor about all the medicines you take, including prescription and non-prescription medicines, vitamins, and herbal supplements. Other medicines can affect how your body handles DETROL. Your doctor may use a lower dose of DETROL if you are taking:

- Certain medicines for fungus or yeast infections
- Certain medicines for bacterial infections
- Sandimmune® (cyclosporine) or Velban® (vinblastine)

Ask your doctor or pharmacist for a list of these medicines, if you are not sure.

Know the medicines you take. Keep a list of them with you to show your doctor or pharmacist each time you get a new medicine.

How should I take DETROL?

- Take DETROL exactly as your doctor tells you to take it.
- Your doctor will tell you how many DETROL Tablets to take and when to take them.
- Do not change your dose unless told to do so by your doctor.
- You can take DETROL with or without food.
- Take DETROL at the same times each day.
- If you miss a dose of DETROL, just take your next regular dose at your next regular time. Do not try to make up for your missed dose.
- If you take too much DETROL, call your doctor, or go to the hospital emergency room right away.

What should I avoid while taking DETROL?

Medicines like DETROL can cause blurred vision, dizziness, and drowsiness. Do not drive, operate machinery, or do other dangerous activities until you know how DETROL affects you.

What are possible side effects of DETROL?

DETROL may cause allergic reactions that may be serious. Symptoms of a serious allergic reaction may include swelling of the face, lips, throat or tongue. If you experience these symptoms, you should stop taking DETROL and get emergency medical help right away.

The most common side effects with DETROL are:

- Dry mouth
- Dizziness
- Headache
- Stomach pain
- Constipation

Tell your doctor if you have any side effects that bother you or that do not go away.

These are not all the side effects with DETROL. For a complete list, ask your doctor or pharmacist.

Call your doctor for medical advice about side effects. You may report side effects to the FDA at 1-800-FDA-1088.

How do I store DETROL?

- Store DETROL at room temperature (59 to 86° F).
- Keep it in a dry place.

Keep DETROL and all medicines out of the reach of children.

General Information about DETROL

Medicines are sometimes prescribed for conditions that are not mentioned in the patient information leaflet. Only use DETROL the way your doctor tells you. Do not give DETROL to other people even if they have the same symptoms you have. It may harm them.

This leaflet summarizes the most important information about DETROL. If you would like more information, talk with your doctor. You can ask your doctor or pharmacist for information about DETROL that is written for health professionals.

For more information, call Viatris at 1-877-446-3679 (1-877-4-INFO-RX).

What are the ingredients in DETROL?
Active ingredients: tolterodine tartrate
Inactive ingredients: colloidal anhydrous silica, calcium hydrogen phosphate dihydrate, cellulose microcrystalline, hypromellose, magnesium stearate, sodium starch glycolate (pH 3.0 to 5.0), stearic acid, and titanium dioxide.

Distributed by:
Viatris Specialty LLC
Morgantown, WV 26505 U.S.A.

Made in Italy

© 2023 Viatris Inc.

DETROL is a registered trademark of Viatris Specialty LLC, a Viatris Company.

The brands listed are trademarks of their respective owners.

UPJ:PL:DTRLT:R1

Revised: 2/2023

PRINCIPAL DISPLAY PANEL – 1 mg

NDC 58151-098-91

Detrol®
tolterodine tartrate
1 mg
tablets

60 Tablets

Rx only

VIATRIS™

Store at 25°C (77°F); excursions
permitted to 15-30°C (59-86°F)
[see USP Controlled Room
Temperature]
Dispense in tight containers (USP).
DOSAGE AND USE:
See accompanying
prescribing information.
Each tablet contains
1 mg tolterodine tartrate.

Distributed by:
Viatris Specialty LLC
Morgantown, WV 26505 U.S.A.

Made in Italy

© 2023 Viatris Inc.

RUPJ098D

PAA208141

PRINCIPAL DISPLAY PANEL – 2 mg

NDC 58151-099-91

Detrol®
tolterodine tartrate
2 mg
tablets

60 Tablets

Rx only

VIATRIS™

Store at 25°C (77°F); excursions
permitted to 15-30°C (59-86°F)
[see USP Controlled Room
Temperature]
Dispense in tight containers (USP).
DOSAGE AND USE:
See accompanying
prescribing information.
Each tablet contains
2 mg tolterodine tartrate.

Distributed by:
Viatris Specialty LLC
Morgantown, WV 26505 U.S.A.

Made in Italy

© 2023 Viatris Inc.

RUPJ099D

PAA208142